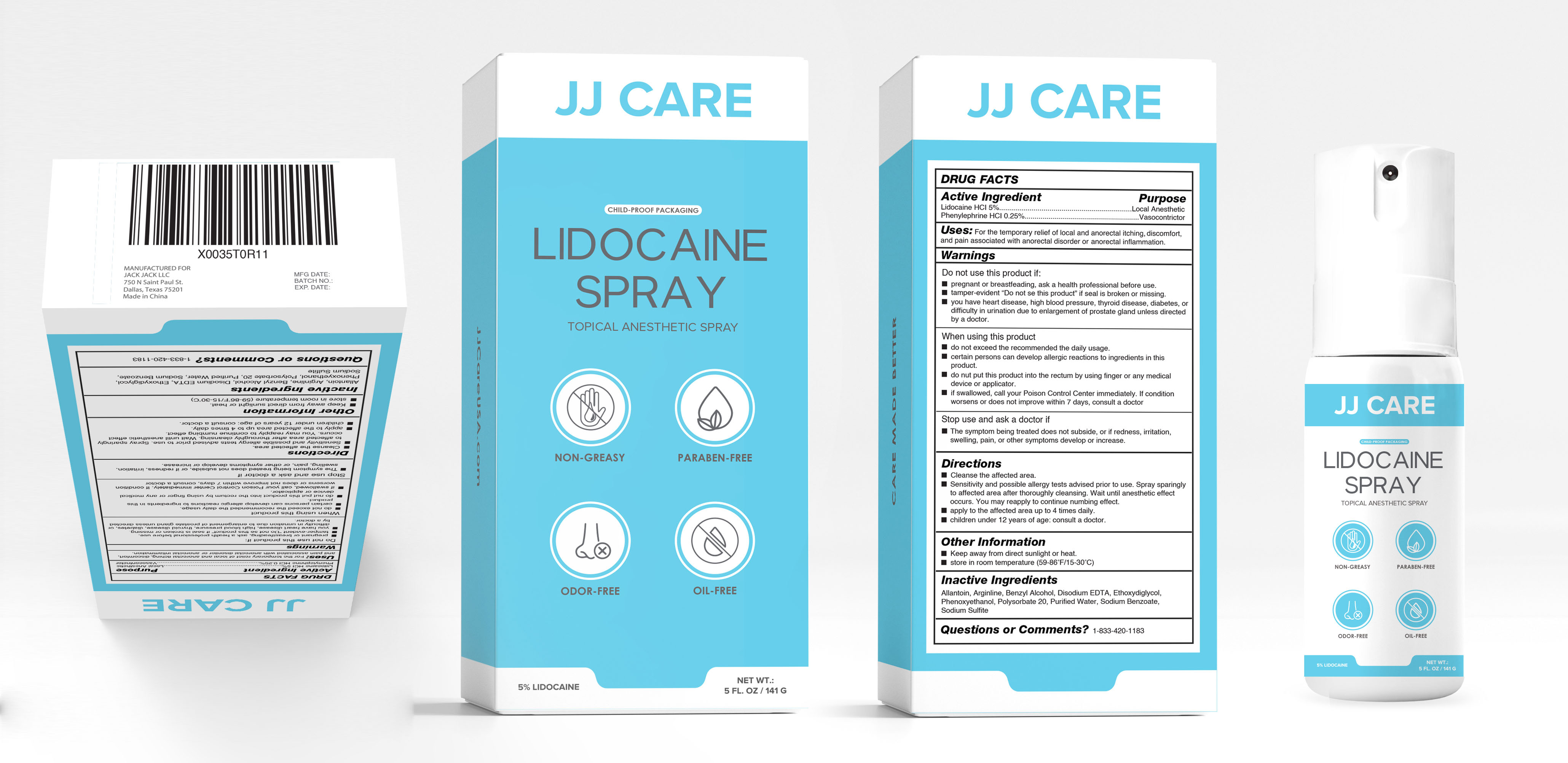 DRUG LABEL: LIDOCAINE
NDC: 83365-002 | Form: SPRAY
Manufacturer: Sichuan Gumo Brand Management Co.,Ltd
Category: otc | Type: HUMAN OTC DRUG LABEL
Date: 20230418

ACTIVE INGREDIENTS: LIDOCAINE 5 g/100 g; PHENYLEPHRINE HYDROCHLORIDE 0.25 g/100 g
INACTIVE INGREDIENTS: PHENOXYETHANOL; POLYSORBATE 20; SODIUM BENZOATE; BENZYL ALCOHOL; EDETATE DISODIUM ANHYDROUS; WATER; SODIUM SULFITE; DIETHYLENE GLYCOL MONOETHYL ETHER; ARGININE; ALLANTOIN

83365-001

Active Ingredient

Lidocaine Hcl 5%

Phenylephrine Hcl 0.25%

Purpose

Local Anesthetic

Vasoconstrictor

Uses

For the temporary relief of local and anorectal itching , discomfortand pain associated with anorectal disorder or anorectal inflammation.

Warnings

Do not use this product if :
pregnant or breastfeeding, ask a health professional before use.
tamper-evident " Do not se this product if seal is broken or missing.
you have heart disease, high blood pressure, thyroid disease, diabetes, or difficulty in urination due to enlargement of prostate gland unless directed by a doctor.

Do not use this product if :
pregnant or breastfeeding, ask a health professional before use.
tamper-evident " Do not se this product if seal is broken or missing.
you have heart disease, high blood pressure, thyroid disease, diabetes, or difficulty in urination due to enlargement of prostate gland unless directed by a doctor.

When using

When using this product
do not exceed the recommended the daily usage.
certain persons can develop allergic reactions to ingredients in this product.
do nut put this product into the rectum by using finger or any medical device or applicator.
If swallowed, call your Poison Control Center immediately. If condition worsens or does not improve within 7 days, consult a doctor

Stop use

Stop use and ask a doctor if
The symptom being treated does not subside, or if redness, irritation, swelling, pain, or other symptoms develop or increase.

Directions

Cleanse the affected area.
Sensitivity and possible allergy tests advised prior to use Spray sparingly to affected area after thoroughly cleansing. Wait until anesthetic effect occurs . You may reapply to continue numbing effect.
apply to the affected area up to 4 times daily.
children under 12 years of age: consult a doctor.

Other Information

Keep away from direct sunlight or heat.
store in room temperature (59-86F/15-30C)

Inactive Ingredients

Allantoin, Arginline, Benzyl Alcohol, Disodium EDTA , Ethoxydiglycol, Phenoxyethanol, Polysorbate 20, Purified Water, Sodium Benzoate, Sodium Sulfite

Keep Out Of Reach Of Children If Swallowed .Get Medical Help Or Contact A Poison Control Center Right Away